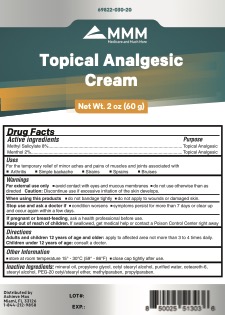 DRUG LABEL: MMM Topical Analgesic Cream
NDC: 69822-030 | Form: CREAM
Manufacturer: Southern Sales & Services, Inc.
Category: otc | Type: HUMAN OTC DRUG LABEL
Date: 20210921

ACTIVE INGREDIENTS: METHYL SALICYLATE 8 g/100 g; MENTHOL 2 g/100 g
INACTIVE INGREDIENTS: STEARYL ALCOHOL; MINERAL OIL; WATER; CETOSTEARYL ALCOHOL; POLYETHYLENE GLYCOL, UNSPECIFIED; METHYLPARABEN; PROPYLPARABEN; PROPYLENE GLYCOL; CETEARETH-6

MMM Topical Analgesic Cream

ACTIVE INGREDIENT

Methyl Salicylate 8%

Menthol 2%

PURPOSE

Topical Analgesic

Stop use and ask a doctor if

- condition worsens
- symptoms persist for more than 7 days or clear up and occur again

If pregnant or breast-feeding: ask a health professional before use.

Keep out of reach of children. If swallowed, get medical help or contact a Poison Control Center Immediately.

WARNINGS

For external use only.

- avoid contact with eyes and mucous membranes
- do not use otherwise than as directed

Caution: Discontinue use if excessive irritation of the skin develops.

When using this product

- do not bandage tightly
- do not apply to wounds or damaged skin.

Stop use and ask a doctor if

- condition worsens
- symptoms persist for more than 7 days or clear up and occur again

If pregnant or breast-feeding: ask a health professional before use.

Keep out of reach of children. If swallowed, get medical help or contact a Poison Control Center Immediately.

INDICATIONS AND USAGE

Temporarily relieves minor aches and pains of muscles and joints due to:

- arthritis
- simple backache
- strains
- sprains
- bruises

Stop use and ask a doctor if

- condition worsens
- symptoms persist for more than 7 days or clear up and occur again

If pregnant or breast-feeding: ask a health professional before use.

Keep out of reach of children. If swallowed, get medical help or contact a Poison Control Center Immediately.

DOSAGE AND ADMINISTRATION

Adults and Children 12 Years of Age or Older: Apply to affected area not more than 3 to 4 times daily.

Children under 12 year of age: consult a doctor

STORAGE AND HANDLING

Store: At Room Temperature 15° - 30°C (59°- 86°F).

Close cap tightly after use.

INACTIVE INGREDIENT

mineral oil, propylene glycol, cetyl stearyl alcohol, purified water, ceteareth-6, stearyl alcohol, PEG-20 cetyl/stearyl ether, methylparaben, propylparaben.